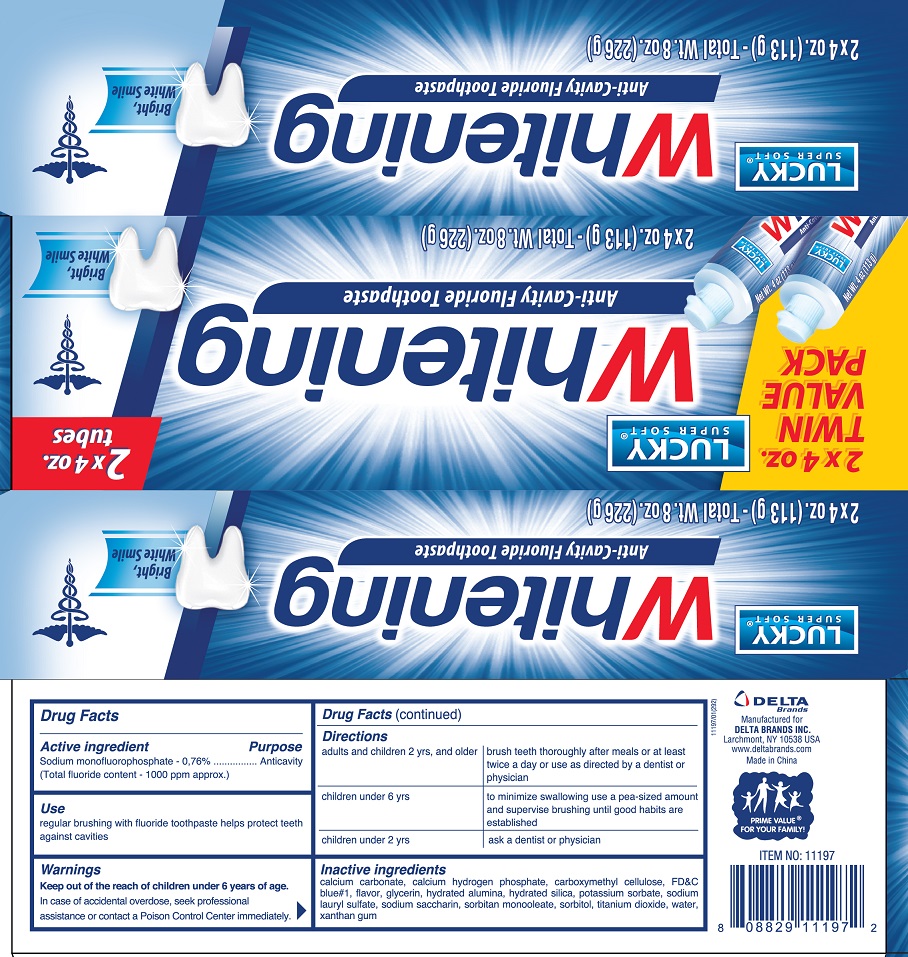 DRUG LABEL: Lucky Super Soft
NDC: 20276-553 | Form: PASTE, DENTIFRICE
Manufacturer: Delta Brands Inc
Category: otc | Type: HUMAN OTC DRUG LABEL
Date: 20181228

ACTIVE INGREDIENTS: SODIUM MONOFLUOROPHOSPHATE 7.6 mg/1 g
INACTIVE INGREDIENTS: POTASSIUM SORBATE; CALCIUM CARBONATE; ANHYDROUS DIBASIC CALCIUM PHOSPHATE; CARBOXYMETHYLCELLULOSE SODIUM; SODIUM SILICATE; SODIUM LAURYL SULFATE; GLYCERIN; ALUMINUM HYDROXIDE; HYDRATED SILICA; FD&C BLUE NO. 1; SORBITAN MONOOLEATE; SACCHARIN SODIUM; SORBITOL; TITANIUM DIOXIDE; WATER; XANTHAN GUM

Drug Facts

Active Ingredient

Sodium monofluorophosphate 0.76% (Total fluoride content-1000 ppm approx.)

Purpose

Anticavity

Use

regular brushing with fluoride tothpaste helps protect against cavities

Keep out of the reach of children

under 6 years of age

Warnings

In case of accidental overdose, seek professional assistance or contact a Poison Control Center immediately

Directions

adults and children 2 yrs and older brush teeth thoroughly after meals or at least twice a day or use as directed by a dentist or physician. children under 6 yrs to minimize swallowing use a pea-sized amount and brushing until good habits are established. children under 2 years: ask a dentist or physician

Inactive ingredients

calcium carbonate, calcium hydrogen phosphate, carboxymethyl cellulose, FDC Blue 1, flavor, glycerin, hydrated alumina, hydrated silica, potassium sorbate, sodium lauryl sulfate, sodium saccharin, sorbitan monooleate, sorbitol, titanium dioxide, water, xanthan gum